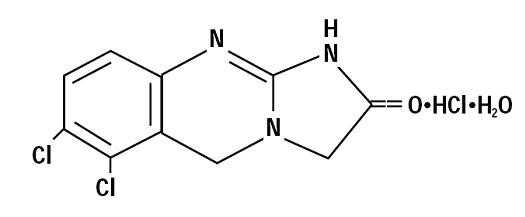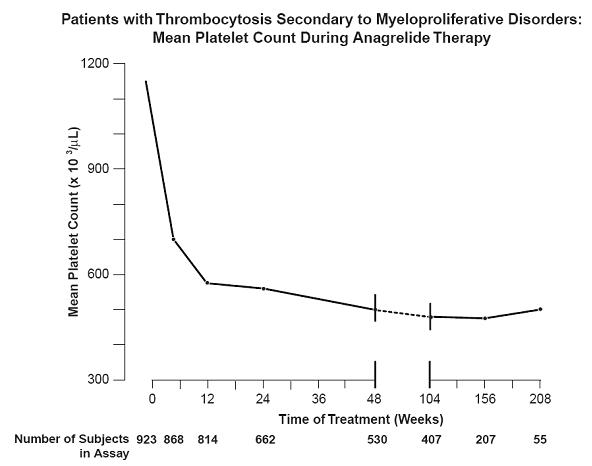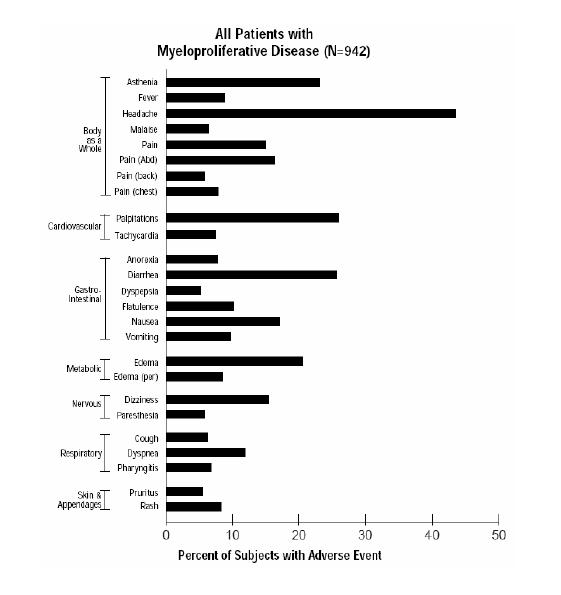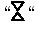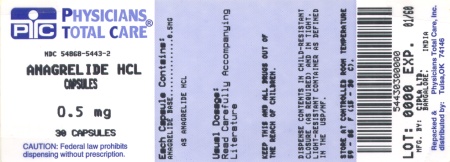 DRUG LABEL: Anagrelide Hydrochloride
NDC: 54868-5443 | Form: CAPSULE
Manufacturer: Physicians Total Care, Inc.
Category: prescription | Type: HUMAN PRESCRIPTION DRUG LABEL
Date: 20120427

ACTIVE INGREDIENTS: Anagrelide Hydrochloride 0.5 mg/1 1
INACTIVE INGREDIENTS: CELLULOSE, MICROCRYSTALLINE; CROSPOVIDONE; D&C YELLOW NO. 10; FD&C BLUE NO. 1; FD&C BLUE NO. 2; FD&C RED NO. 40; ALUMINUM OXIDE; FERROSOFERRIC OXIDE; GELATIN; ANHYDROUS LACTOSE; LACTOSE MONOHYDRATE; MAGNESIUM STEARATE; POVIDONE; PROPYLENE GLYCOL; TITANIUM DIOXIDE

ANAGRELIDE HYDROCHLORIDE CAPSULES
Rx only

DESCRIPTION

Anagrelide hydrochloride is an off white powder that is very slightly soluble in water and sparingly soluble in dimethyl sulfoxide and in dimethylformamide. Anagrelide hydrochloride is a platelet-reducing agent with a chemical name of 6,7-dichloro-1,5-dihydroimidazo[2,1-b] quinazolin-2(3H)-one monohydrochloride monohydrate, and it has the following structural formula:

C10H7Cl2N3O·HCl·H2O M.W. 310.55

Each anagrelide hydrochloride capsule, for oral administration, contains either 0.5 mg or 1 mg of anagrelide base (as anagrelide hydrochloride) and has the following inactive ingredients: black iron oxide, crospovidone, D&C yellow #10 aluminum lake, FD&C blue #1/brilliant blue aluminum lake, FD&C blue #2/indigo carmine aluminum lake, FD&C red #40/allura red aluminum lake, gelatin, lactose anhydrous, lactose monohydrate, magnesium stearate, microcrystalline cellulose, povidone, propylene glycol, shellac glaze and titanium dioxide.

CLINICAL PHARMACOLOGY

The mechanism by which anagrelide reduces blood platelet count is still under investigation. Studies in patients support a hypothesis of dose-related reduction in platelet production resulting from a decrease in megakaryocyte hypermaturation. In blood withdrawn from normal volunteers treated with anagrelide, a disruption was found in the postmitotic phase of megakaryocyte development and a reduction in megakaryocyte size and ploidy. At therapeutic doses, anagrelide does not produce significant changes in white cell counts or coagulation parameters, and may have a small, but clinically insignificant effect on red cell parameters. Anagrelide inhibits cyclic AMP phosphodiesterase III (PDEIII). PDEIII inhibitors can also inhibit platelet aggregation. However, significant inhibition of platelet aggregation is observed only at doses of anagrelide higher than those required to reduce platelet count.

Following oral administration of ^14C-anagrelide in people, more than 70% of radioactivity was recovered in urine. Based on limited data, there appears to be a trend toward dose linearity between doses of 0.5 mg and 2 mg. At fasting and at a dose of 0.5 mg of anagrelide, the plasma half-life is 1.3 hours. The available plasma concentration time data at steady state in patients showed that anagrelide does not accumulate in plasma after repeated administration.

Two major metabolites have been identified (RL603 and 3-hydroxy anagrelide).

There were no apparent differences between patient groups (pediatric versus adult patients) for tmax and for t1/2 for anagrelide, 3-hydroxy anagrelide, or RL603.

Pharmacokinetic data obtained from healthy volunteers comparing the pharmacokinetics of anagrelide in the fed and fasted states showed that administration of a 1 mg dose of anagrelide with food decreased the Cmax by 14%, but increased the AUC by 20%.

Pharmacokinetic (PK) data from pediatric (age range 7 to 14 years) and adult (age range 16 to 86 years) patients with thrombocythemia secondary to a myeloproliferative disorder (MPD), indicate that dose- and body weight-normalized exposure, Cmax and AUCτ, of anagrelide were lower in the pediatric patients compared to the adult patients (Cmax 48%, AUCτ 55%).

Pharmacokinetic data from fasting elderly patients with ET (age range 65 to 75 years) compared to fasting adult patients (age range 22 to 50 years) indicate that the Cmax and AUC of anagrelide were 36% and 61% higher respectively in elderly patients, but that the Cmax and AUC of the active metabolite, 3-hydroxy anagrelide, were 42% and 37% lower respectively in the elderly patients.

A pharmacokinetic study at a single dose of 1 mg anagrelide in subjects with severe renal impairment (creatinine clearance < 30 mL/min) showed no significant effects on the pharmacokinetics of anagrelide.

A pharmacokinetic study at a single dose of 1 mg anagrelide in subjects with moderate hepatic impairment showed an 8 fold increase in total exposure (AUC) to anagrelide.

CLINICAL STUDIES

A total of 942 patients with myeloproliferative disorders including 551 patients with Essential Thrombocythemia (ET), 117 patients with Polycythemia Vera (PV), 178 patients with Chronic Myelogenous Leukemia (CML), and 96 patients with other myeloproliferative disorders (OMPD), were treated with anagrelide in three clinical trials. Patients with OMPD included 87 patients who had Myeloid Metaplasia with Myelofibrosis (MMM), and 9 patients who had unknown myeloproliferative disorders.

Clinical Studies

Patients with ET, PV, CML, or MMM were diagnosed based on the following criteria:

ET:

- Platelet count ≥ 900,000/µL on two determinations
- Profound megakaryocytic hyperplasia in bone marrow
- Absence of Philadelphia chromosome
- Normal red cell mass
- Normal serum iron and ferritin and normal marrow iron stores

CML:

- Persistent granulocyte count ≥ 50,000/µL without evidence of infection
- Absolute basophil count ≥ 100/µL
- Evidence for hyperplasia of the granulocytic line in the bone marrow
- Philadelphia chromosome is present
- Leukocyte alkaline phosphatase ≤ lower limit of the laboratory normal range

PV†:

- A1 Increased red cell mass
- A2 Normal arterial oxygen saturation
- A3 Splenomegaly
- B1 Platelet count ≥ 400,000/µL, in absence of iron deficiency or bleeding
- B2 Leukocytosis (≥ 12,000/µL, in the absence of infection)
- B3 Elevated leukocyte alkaline phosphatase
- B4 Elevated Serum B12

†Diagnosis positive if A1, A2, and A3 present; or, if no splenomegaly, diagnosis is positive if A1 and A2 are present with any two of B1, B2, or B3.

MMM:

- Myelofibrotic (hypocellular, fibrotic) bone marrow
- Prominent megakaryocytic metaplasia in bone marrow
- Splenomegaly
- Moderate to severe normo-chromic normocytic anemia
- White cell count may be variable; (80,000 to 100,000/µL)
- Increased platelet count
- Variable red cell mass; teardrop poikilocytes
- Normal to high leukocyte alkaline phosphatase
- Absence of Philadelphia chromosome

Patients were enrolled in clinical trials if their platelet count was ≥ 900,000/µL on two occasions or ≥ 650,000/µL on two occasions with documentation of symptoms associated with thrombocythemia. The mean duration of anagrelide therapy for ET, PV, CML, and OMPD patients was 65, 67, 40, and 44 weeks, respectively; 23% of patients received treatment for 2 years. Patients were treated with anagrelide starting at doses of 0.5 to 2 mg every 6 hours. The dose was increased if the platelet count was still high, but to no more than 12 mg each day. Efficacy was defined as reduction of platelet count to or near physiologic levels (150,000 to 400,000/µL). The criteria for defining subjects as "responders" were reduction in platelets for at least 4 weeks to ≤600,000/µL, or by at least 50% from baseline value. Subjects treated for less than 4 weeks were not considered evaluable. The results are depicted graphically below:

 |  | Time on Treatment
 |  | Weeks |  |  |  |  | Years
 | Baseline |  | 4 | 12 | 24 | 48 | 2 | 3 | 4
Mean* | 1131 |  | 683 | 575 | 526 | 484 | 460 | 437 | 457
N | 923 ** |  | 868 | 814 | 662 | 530 | 407 | 207 | 55
* x10^3/µL
** Nine hundred and forty-two subjects with myeloproliferative disorders were enrolled in three research studies. Of these, 923 had platelet counts over the duration of the studies.

Anagrelide was effective in phlebotomized patients as well as in patients treated with other concomitant therapies including hydroxyurea, aspirin, interferon, radioactive phosphorus, and alkylating agents.

INDICATIONS AND USAGE

Anagrelide hydrochloride capsules are indicated for the treatment of patients with thrombocythemia, secondary to myeloproliferative disorders, to reduce the elevated platelet count and the risk of thrombosis and to ameliorate associated symptoms including thrombo-hemorrhagic events (see CLINICAL STUDIES, DOSAGE AND ADMINISTRATION).

CONTRAINDICATIONS

Anagrelide is contraindicated in patients with severe hepatic impairment. Exposure to anagrelide is increased 8 fold in patients with moderate hepatic impairment (see CLINICAL PHARMACOLOGY). Use of anagrelide in patients with severe hepatic impairment has not been studied (see also WARNINGS, Hepatic).

WARNINGS

Cardiovascular

Anagrelide should be used with caution in patients with known or suspected heart disease, and only if the potential benefits of therapy outweigh the potential risks. Because of the positive inotropic effects and side effects of anagrelide, a pre-treatment cardiovascular examination is recommended along with careful monitoring during treatment. In humans, therapeutic doses of anagrelide may cause cardiovascular effects, including vasodilation, tachycardia, palpitations, and congestive heart failure.

Hepatic

Exposure to anagrelide is increased 8 fold in patients with moderate hepatic impairment (see CLINICAL PHARMACOLOGY). Use of anagrelide in patients with severe hepatic impairment has not been studied. The potential risks and benefits of anagrelide therapy in a patient with mild and moderate impairment of hepatic function should be assessed before treatment is commenced. In patients with moderate hepatic impairment, dose reduction is required and patients should be carefully monitored for cardiovascular effects (see DOSAGE AND ADMINISTRATION for specific dosing recommendations).

Interstitial lung diseases (including allergic alveolitis, eosinophilic pneumonia and interstitial pneumonitis) have been reported to be associated with the use of anagrelide in postmarketing reports. Most cases presented with progressive dyspnea with lung infiltrations. The time of onset ranged from 1 week to several years after initiating anagrelide. In most cases, the symptoms improved after discontinuation of anagrelide (see ADVERSE REACTIONS).

PRECAUTIONS

Laboratory Tests

Anagrelide therapy requires close clinical supervision of the patient. While the platelet count is being lowered (usually during the first two weeks of treatment), blood counts (hemoglobin, white blood cells) and renal function (serum creatinine, BUN) should be monitored. Cases of clinically significant hepatotoxicity (including symptomatic ALT and AST elevations and elevations greater than three times the ULN) have been reported in postmarketing surveillance. Measure liver function tests (ALT, AST) before initiating anagrelide treatment and during therapy.

In 9 subjects receiving a single 5 mg dose of anagrelide, standing blood pressure fell an average of 22/15 mm Hg, usually accompanied by dizziness. Only minimal changes in blood pressure were observed following a dose of 2 mg.

Cessation of Anagrelide Treatment

In general, interruption of anagrelide treatment is followed by an increase in platelet count. After sudden stoppage of anagrelide therapy, the increase in platelet count can be observed within four days.

Drug Interactions

Limited PK and/or PD studies investigating possible interactions between anagrelide and other medicinal products have been conducted. In vivo interaction studies in humans have demonstrated that digoxin and warfarin do not affect the PK properties of anagrelide, nor does anagrelide affect the PK properties of digoxin or warfarin.

In two clinical interaction studies in healthy subjects, coadministration of single-dose anagrelide 1 mg and aspirin 900 mg or repeat-dose anagrelide 1 mg once daily and aspirin 75 mg once daily showed greater ex vivo anti-platelet aggregation effects than administration of aspirin alone. Coadministered anagrelide 1 mg and aspirin 900 mg single-doses had no effect on bleeding time, prothrombin time (PT) or activated partial thromboplastin time (aPTT).

The potential risks and benefits of concomitant use of anagrelide with aspirin should be assessed, particularly in patients with a high risk profile for hemorrhage, before treatment is commenced.

Drug interaction studies have not been conducted with the other common medications used concomitantly with anagrelide in clinical trials which were acetaminophen, furosemide, iron, ranitidine, hydroxyurea, and allopurinol.

Anagrelide is metabolized at least in part by CYP1A2. It is known that CYP1A2 is inhibited by several medicinal products, including fluvoxamine, and such medicinal products could theoretically adversely influence the clearance of anagrelide. Anagrelide demonstrates some limited inhibitory activity towards CYP1A2 which may present a theoretical potential for interaction with other coadministered medicinal products sharing that clearance mechanism e.g., theophylline.

Anagrelide is an inhibitor of cyclic AMP PDE III. The effects of medicinal products with similar properties such as inotropes milrinone, enoximone, amrinone, olprinone and cilostazol may be exacerbated by anagrelide.

There is a single case report which suggests that sucralfate may interfere with anagrelide absorption.

Food has no clinically significant effect on the bioavailability of anagrelide.

Carcinogenesis, Mutagenesis, Impairment of Fertility

In a two year rat carcinogenicity study a higher incidence of uterine adenocarcinoma, relative to controls, was observed in females receiving 30 mg/kg/day (at least 174 times human AUC exposure after a 1 mg twice daily dose). Adrenal phaeochromocytomas were increased relative to controls in males receiving 3 mg/kg/day and above, and in females receiving 10 mg/kg/day and above (at least 10 and 18 times respectively human AUC exposure after a 1 mg twice daily dose). Anagrelide hydrochloride was not genotoxic in the Ames test, the mouse lymphoma cell (L5178Y, TK+/-) forward mutation test, the human lymphocyte chromosome aberration test, or the mouse micronucleus test. Anagrelide hydrochloride at oral doses up to 240 mg/kg/day (1,440 mg/m^2/day, 195 times the recommended maximum human dose based on body surface area) was found to have no effect on fertility and reproductive performance of male rats. However, in female rats, at oral doses of 60 mg/kg/day (360 mg/m^2/day, 49 times the recommended maximum human dose based on body surface area) or higher, it disrupted implantation when administered in early pregnancy and retarded or blocked parturition when administered in late pregnancy.

Pregnancy

Pregnancy Category C

Teratogenic Effects

Teratology studies have been performed in pregnant rats at oral doses up to 900 mg/kg/day (5,400 mg/m^2/day, 730 times the recommended maximum human dose based on body surface area) and in pregnant rabbits at oral doses up to 20 mg/kg/day (240 mg/m^2/day, 32 times the recommended maximum human dose based on body surface area) and have revealed no evidence of impaired fertility or harm to the fetus due to anagrelide hydrochloride.

Nonteratogenic Effects

A fertility and reproductive performance study performed in female rats revealed that anagrelide hydrochloride at oral doses of 60 mg/kg/day (360 mg/m^2/day, 49 times the recommended maximum human dose based on body surface area) or higher disrupted implantation and exerted adverse effect on embryo/fetal survival.

A perinatal and postnatal study performed in female rats revealed that anagrelide hydrochloride at oral doses of 60 mg/kg/day (360 mg/m^2/day, 49 times the recommended maximum human dose based on body surface area) or higher produced delay or blockage of parturition, deaths of non-delivering pregnant dams and their fully developed fetuses, and increased mortality in the pups born.

There are however no adequate and well-controlled studies with anagrelide hydrochloride in pregnant women. Because animal reproduction studies are not always predictive of human response, anagrelide hydrochloride should be used during pregnancy only if clearly needed.

Nonclinical Toxicology

In the 2-year rat study, a significant increase in non-neoplastic lesions were observed in anagrelide treated males and females in the adrenal (medullary hyperplasia), heart (myocardial hypertrophy and chamber distension), kidney (hydronephrosis, tubular dilation and urothelial hyperplasia) and bone (femur enostosis). Vascular effects were observed in tissues of the pancreas (arteritis/periarteritis, intimal proliferation and medial hypertrophy), kidney (arteritis/periarteritis, intimal proliferation and medial hypertrophy), sciatic nerve (vascular mineralization), and testes (tubular atrophy and vascular infarct) in anagrelide treated males.

Five women became pregnant while on anagrelide treatment at doses of 1 to 4 mg/day. Treatment was stopped as soon as it was realized that they were pregnant. All delivered normal, healthy babies. There are no adequate and well-controlled studies in pregnant women. Anagrelide hydrochloride should be used during pregnancy only if the potential benefit justifies the potential risk to the fetus.

Anagrelide is not recommended in women who are or may become pregnant. If this drug is used during pregnancy, or if the patient becomes pregnant while taking this drug, the patient should be apprised of the potential harm to the fetus. Women of child-bearing potential should be instructed that they must not be pregnant and that they should use contraception while taking anagrelide. Anagrelide may cause fetal harm when administered to a pregnant woman.

Nursing Mothers

It is not known whether this drug is excreted in human milk. Because many drugs are excreted in human milk and because of the potential for serious adverse reaction in nursing infants from anagrelide hydrochloride, a decision should be made whether to discontinue nursing or to discontinue the drug, taking into account the importance of the drug to the mother.

Pediatric Use

Myeloproliferative disorders are uncommon in pediatric patients and limited data are available in this population. An open label safety and PK/PD study (see CLINICAL PHARMACOLOGY) was conducted in 17 pediatric patients 7 to 14 years of age (8 patients 7 to 11 years of age and 9 patients 11 to 14 years of age, mean age of 11 years; 8 males and 9 females) with thrombocythemia secondary to ET as compared to 18 adult patients (mean age of 63 years, 9 males and 9 females). Prior to entry on to the study, 16 of 17 pediatric patients and 13 of 18 adult patients had received anagrelide treatment for an average of 2 years. The median starting total daily dose, determined by retrospective chart review, for pediatric and adult ET patients who had received anagrelide prior to study entry was 1 mg for each of the three age groups (7 to 11 and 11 to 14 year old patients and adults). The starting dose for 6 anagrelide-naive patients at study entry was 0.5 mg once daily. At study completion, the median total daily maintenance doses were similar across age groups, median of 1.75 mg for patients of 7 to 11 years of age, 2 mg in patients 11 to 14 years of age, and 1.5 mg for adults.

The study evaluated the pharmacokinetic (PK) and pharmacodynamic (PD) profile of anagrelide, including platelet counts (see CLINICAL PHARMACOLOGY).

The frequency of adverse events observed in pediatric patients was similar to adult patients. The most common adverse events observed in pediatric patients were fever, epistaxis, headache, and fatigue during a 3 months treatment of anagrelide in the study. Adverse events that had been reported in these pediatric patients prior to the study and were considered to be related to anagrelide treatment based on retrospective review were palpitation, headache, nausea, vomiting, abdominal pain, back pain, anorexia, fatigue, and muscle cramps. Episodes of increased pulse rate and decreased systolic or diastolic blood pressure beyond the normal ranges in the absence of clinical symptoms were observed in some patients. Reported AEs were consistent with the known pharmacological profile of anagrelide and the underlying disease. There were no apparent trends or differences in the types of adverse events observed between the pediatric patients compared with those of the adult patients. No overall difference in dosing and safety were observed between pediatric and adult patients.

In another open-label study, anagrelide had been used successfully in 12 pediatric patients (age range 6.8 to 17.4 years; 6 male and 6 female), including 8 patients with ET, 2 patients with CML, 1 patient with PV, and 1 patient with OMPD. Patients were started on therapy with 0.5 mg q.i.d. up to a maximum daily dose of 10 mg. The median duration of treatment was 18.1 months with a range of 3.1 to 92 months. Three patients received treatment for greater than three years. Other adverse events reported in spontaneous reports and literature reviews include anemia, cutaneous photosensitivity and elevated leukocyte count.

Geriatric Use

Of the total number of subjects in clinical studies of anagrelide, 42.1% were 65 years and over, while 14.9% were 75 years and over. No overall differences in safety or effectiveness were observed between these subjects and younger subjects, and other reported clinical experience has not identified differences in response between the elderly and younger patients, but greater sensitivity of some older individuals cannot be ruled out.

ADVERSE REACTIONS

Analysis of the adverse events in a population consisting of 942 patients in 3 clinical studies diagnosed with myeloproliferative diseases of varying etiology (ET: 551; PV: 117; OMPD: 274) has shown that all disease groups have the same adverse event profile. While most reported adverse events during anagrelide therapy have been mild in intensity and have decreased in frequency with continued therapy, serious adverse events were reported in these patients. These include the following: congestive heart failure, myocardial infarction, cardiomyopathy, cardiomegaly, complete heart block, atrial fibrillation, cerebrovascular accident, pericarditis, pericardial effusion, pleural effusion, pulmonary infiltrates, pulmonary fibrosis, pulmonary hypertension, pancreatitis, gastric/duodenal ulceration, and seizure.

Of the 942 patients treated with anagrelide for a mean duration of approximately 65 weeks, 161 (17%) were discontinued from the study because of adverse events or abnormal laboratory test results. The most common adverse events for treatment discontinuation were headache, diarrhea, edema, palpitation, and abdominal pain. Overall, the occurrence rate of all adverse events was 17.9 per 1,000 treatment days. The occurrence rate of adverse events increased at higher dosages of anagrelide.

The most frequently reported adverse reactions to anagrelide (in 5% or greater of 942 patients with myeloproliferative disease) in clinical trials were:

Headache…………………………………….. | 43.5%
Palpitations…………………………………... | 26.1%
Diarrhea……………………………………… | 25.7%
Asthenia……………………………………… | 23.1%
Edema, other…………………………………. | 20.6%
Nausea……………………………………….. | 17.1%
Abdominal pain……………………………… | 16.4%
Dizziness…………………………………….. | 15.4%
Pain, other……………………………………. | 15%
Dyspnea……………………………………… | 11.9%
Flatulence……………………………………. | 10.2%
Vomiting……………………………………... | 9.7%
Fever…………………………………………. | 8.9%
Peripheral edema……………………………. | 8.5%
Rash, including urticaria…………………….. | 8.3%
Chest pain……………………………………. | 7.8%
Anorexia……………………………………... | 7.7%
Tachycardia………………………………….. | 7.5%
Pharyngitis…………………………………… | 6.8%
Malaise………………………………………. | 6.4%
Cough………………………………………... | 6.3%
Paresthesia…………………………………… | 5.9%
Back pain…………………………………….. | 5.9%
Pruritus………………………………………. | 5.5%
Dyspepsia……………………………………. | 5.2%

Adverse events with an incidence of 1% to < 5% included:

Body as a Whole System

Flu symptoms, chills, photosensitivity

Cardiovascular System

Arrhythmia, hemorrhage, hypertension, cardiovascular disease, angina pectoris, heart failure, postural hypotension, thrombosis, vasodilatation, migraine, syncope

Digestive System

Constipation, GI distress, GI hemorrhage, gastritis, melena, aphthous stomatitis, eructation

Hemic and Lymphatic System

Anemia, thrombocytopenia, ecchymosis, lymphadenopathy

Platelet counts below 100,000/µL occurred in 84 patients (ET: 35; PV: 9; OMPD: 40), reduction below 50,000/µL occurred in 44 patients (ET: 7; PV: 6; OMPD: 31) while on anagrelide therapy. Thrombocytopenia promptly recovered upon discontinuation of anagrelide.

Hepatic System

Elevated liver enzymes were observed in 3 patients (ET: 2; OMPD: 1) during anagrelide therapy.

Musculoskeletal System

Arthralgia, myalgia, leg cramps

Nervous System

Depression, somnolence, confusion, insomnia, nervousness, amnesia

Nutritional Disorders

Dehydration

Respiratory System

Rhinitis, epistaxis, respiratory disease, sinusitis, pneumonia, bronchitis, asthma

Skin and Appendages System

Skin disease, alopecia

Special Senses

Amblyopia, abnormal vision, tinnitus, visual field abnormality, diplopia

Urogenital System

Dysuria, hematuria

Renal abnormalities occurred in 15 patients (ET: 10; PV: 4; OMPD: 1). Six ET, 4 PV and 1 with OMPD experienced renal failure (approximately 1%) while on anagrelide treatment; in 4 cases, the renal failure was considered to be possibly related to anagrelide treatment. The remaining 11 were found to have pre-existing renal impairment. Doses ranged from 1.5 to 6 mg/day, with exposure periods of 2 to 12 months. No dose adjustment was required because of renal insufficiency.

The adverse event profile for patients in three clinical trials on anagrelide therapy (in 5% or greater of 942 patients with myeloproliferative diseases) is shown in the following bar graph:

Postmarketing Reports

Cases of interstitial lung diseases (including allergic alveolitis, eosinophilic pneumonia and interstitial pneumonitis), tubulointerstitial nephritis and clinically significant hepatotoxicity have been reported (see WARNINGS, Interstitial Lung Diseases and PRECAUTIONS, Laboratory Tests).

OVERDOSAGE

Acute Toxicity and Symptoms

Single oral doses of anagrelide hydrochloride at 2,500, 1,500 and 200 mg/kg in mice, rats and monkeys, respectively, were not lethal. Symptoms of acute toxicity were: decreased motor activity in mice and rats and softened stools and decreased appetite in monkeys.

There have been postmarketing case reports of intentional overdose with anagrelide hydrochloride. Reported symptoms include sinus tachycardia and vomiting. Symptoms resolved with conservative management. Platelet reduction from anagrelide therapy is dose-related; therefore, thrombocytopenia, which can potentially cause bleeding, is expected from overdosage. Should overdosage occur, cardiac and central nervous system toxicity can also be expected.

Management and Treatment

In case of overdosage, close clinical supervision of the patient is required; this especially includes monitoring of the platelet count for thrombocytopenia. Dosage should be decreased or stopped, as appropriate, until the platelet count returns to within the normal range.

DOSAGE AND ADMINISTRATION

Treatment with anagrelide hydrochloride capsules should be initiated under close medical supervision. The recommended starting dosage of anagrelide hydrochloride capsules for adult patients is 0.5 mg q.i.d. or 1 mg b.i.d (2 capsules of 0.5 mg twice a day), which should be maintained for at least one week. Starting doses in pediatric patients have ranged from 0.5 mg per day to 0.5 mg q.i.d. As there are limited data on the appropriate starting dose for pediatric patients, an initial dose of 0.5 mg per day is recommended. In both adult and pediatric patients, dosage should then be adjusted to the lowest effective dosage required to reduce and maintain platelet count below 600,000/µL, and ideally to the normal range. The dosage should be increased by not more than 0.5 mg/day in any one week. Maintenance dosing is not expected to be different between adult and pediatric patients. Dosage should not exceed 10 mg/day or 2.5 mg in a single dose (see PRECAUTIONS).

There are no special requirements for dosing the geriatric population.

It is recommended that patients with moderate hepatic impairment start anagrelide therapy at a dose of 0.5 mg/day and be maintained for a minimum of one week with careful monitoring of cardiovascular effects. The dosage increment must not exceed more than 0.5 mg/day in any one week. The potential risks and benefits of anagrelide therapy in a patient with mild or moderate impairment of hepatic function should be assessed before treatment is commenced. Use of anagrelide in patients with severe hepatic impairment has not been studied. Use of anagrelide in patients with severe hepatic impairment is contraindicated (see CONTRAINDICATIONS).

To monitor the effect of anagrelide and prevent the occurrence of thrombocytopenia, platelet counts should be performed every two days during the first week of treatment and at least weekly thereafter until the maintenance dosage is reached.

Typically, platelet count begins to respond within 7 to 14 days at the proper dosage. The time to complete response, defined as platelet count ≤600,000/µL, ranged from 4 to 12 weeks. Most patients will experience an adequate response at a dose of 1.5 to 3 mg/day. Patients with known or suspected heart disease, renal insufficiency, or hepatic dysfunction should be monitored closely.

HOW SUPPLIED

Anagrelide Hydrochloride Capsules are available as light gray cap/white body hard gelatin capsules, spin printed in black ink

“5241” on the cap and "0.5 mg" on the body containing 0.5 mg of anagrelide base (as anagrelide hydrochloride) packaged in bottles of 30 capsules.

PHARMACIST: Dispense in a tight, light-resistant container as defined in the USP, with a child-resistant closure (as required).

Store at 20° to 25°C (68° to 77°F) [See USP Controlled Room Temperature].

Manufactured In India By:

Cipla Ltd.

Goa, India

Manufactured For:

TEVA PHARMACEUTICALS USA

Sellersville, PA 18960

Rev. C 2/2011

ANAGRELIDE HYDROCHLORIDE CAPSULES

Relabeling and Repackaging by:
Physicians Total Care, Inc.
Tulsa, Oklahoma 74146

PRINCIPAL DISPLAY PANEL

Anagrelide 0.5 mg Text

ANAGRELIDE

HYDROCHLORIDE

Capsules

0.5 mg

PLATELET-REDUCING AGENT

Rx only